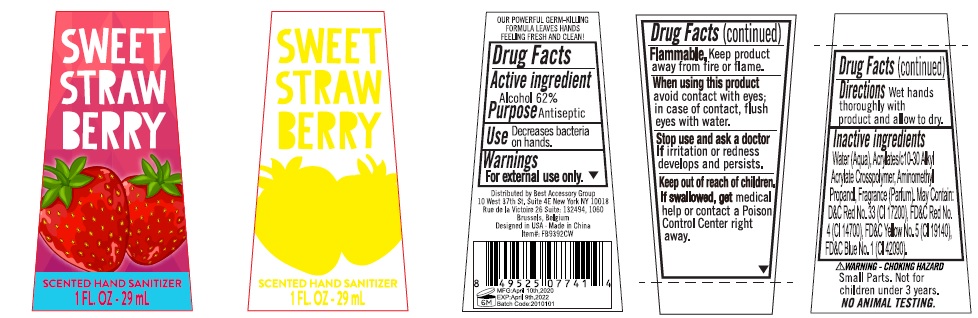 DRUG LABEL: SWEET STRAWBERRY SCENTED HAND SANITIZER
NDC: 56136-030 | Form: SOLUTION
Manufacturer: Ganzhou Olivee Cosmetic Co., Ltd.
Category: otc | Type: HUMAN OTC DRUG LABEL
Date: 20200327

ACTIVE INGREDIENTS: ALCOHOL 62 mL/100 mL
INACTIVE INGREDIENTS: WATER; CARBOMER INTERPOLYMER TYPE A (ALLYL SUCROSE CROSSLINKED); AMINOMETHYLPROPANOL

BEST ACCESSORY GROUP SWEET STRAWBERRY SCENTED HAND SANITIZER

Active ingredient

Alcohol 62%

Purpose

Antiseptic

Use

Decreases bacteria on hands.

Warnings

For external use only.

Flammable,

Keep product away from fire or flame.

When using this product

avoid contact with eyes; in case of contact, flush eyes with water.

Stop use and ask a doctor if

irritation or redness develops and persists.

Keep out of reach of children.

If swallowed, get medical help or contact a Poison Control Center right away.

Directions

Wet hands thoroughly with product and allow to dry.

Inactive ingredients

Water (Aqua), Acrylates/C10-30 Alkyl Acrylate Crosspolymer, Aminomethyl Propanol, Fragrance (Parfum). May Contain: D&C Red No.33 (CI 17200), FD&C Red No.4 (CI 14700), FD&C Yellow No.5 (CI 19140), FD&C Blue No.1 (CI 42090).

OUR POWERFUL GERM-KILLING FORMULA LEAVES HANDS FEELING FRESH AND CLEAN!

Distributed by Best Accessory Group

10 West 37th St. Suite 4E New York NY 10018

Rue de la Victoire 26 Suite: 132494, 1060

Brussels, Belgium

Designed in USA . Made in China

WARNING - CHOKING HAZARD

Small Parts. Not for children under 3 years.

NO ANIMAL TESTING.

NEW!

2 in 1

Anti - Bacterial Sanitizer with Holder

www.mybeautyspot.com